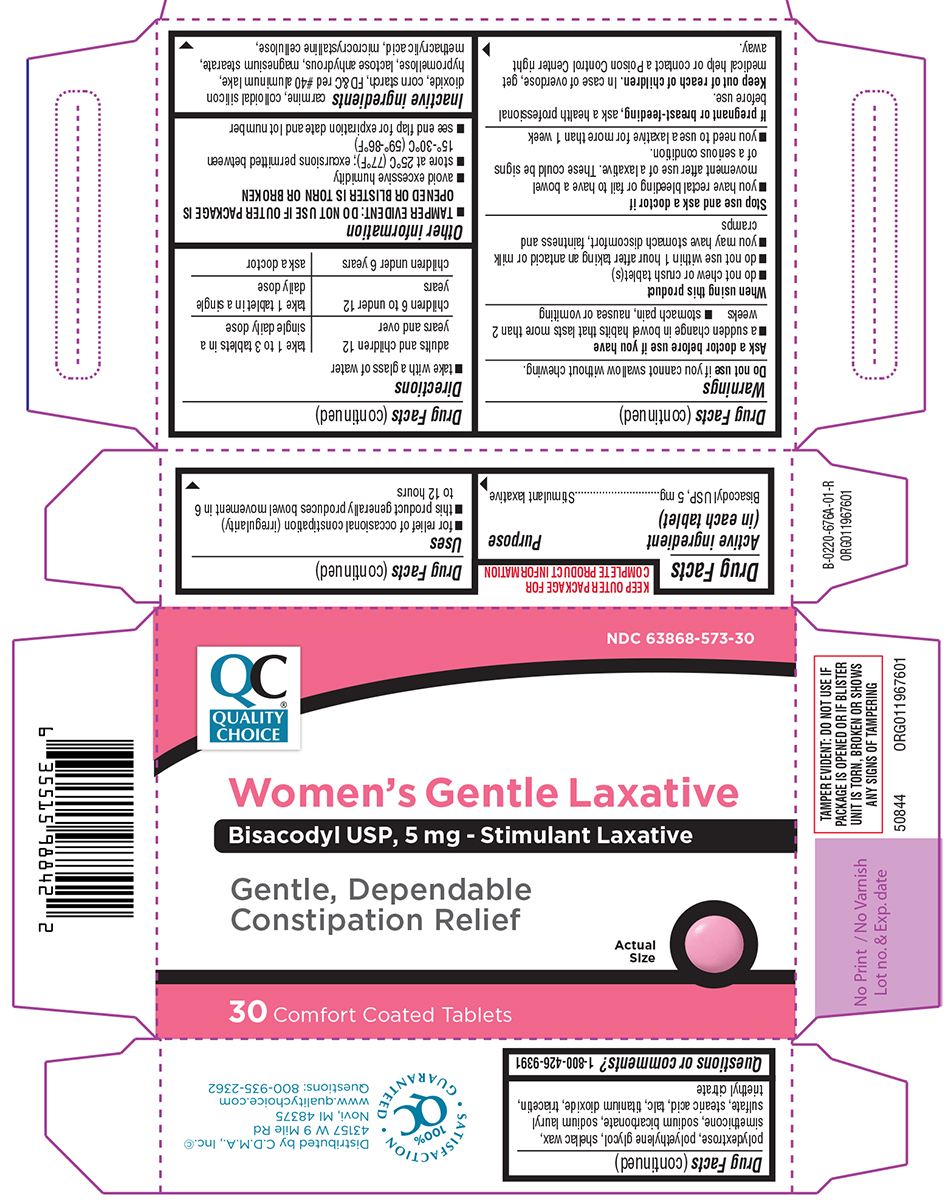 DRUG LABEL: Womens Gentle Laxative
NDC: 63868-573 | Form: TABLET, DELAYED RELEASE
Manufacturer: CHAIN DRUG MARKETING ASSOCIATION INC
Category: otc | Type: HUMAN OTC DRUG LABEL
Date: 20260225

ACTIVE INGREDIENTS: BISACODYL 5 mg/1 1
INACTIVE INGREDIENTS: SILICON DIOXIDE; STARCH, CORN; FD&C RED NO. 40; HYPROMELLOSE, UNSPECIFIED; ANHYDROUS LACTOSE; MAGNESIUM STEARATE; METHACRYLIC ACID; MICROCRYSTALLINE CELLULOSE; POLYDEXTROSE; POLYETHYLENE GLYCOL, UNSPECIFIED; SHELLAC; DIMETHICONE; WATER; SODIUM BICARBONATE; SODIUM LAURYL SULFATE; STEARIC ACID; TALC; TITANIUM DIOXIDE; TRIACETIN; TRIETHYL CITRATE

Quality Choice 44-676A-Delisted

Active ingredient (in each tablet)

Bisacodyl USP, 5 mg

Purpose

Stimulant laxative

Uses

- for relief of occasional constipation (irregularity)
- this product generally produces bowel movement in 6 to 12 hours

Warnings

Do not use

if you cannot swallow without chewing.

Ask a doctor before use if you have

- a sudden change in bowel habits that lasts more than 2 weeks
- stomach pain, nausea or vomiting

When using this product

- do not chew or crush tablet(s)
- do not use within 1 hour after taking an antacid or milk
- you may have stomach discomfort, faintness and cramps

Stop use and ask a doctor if

- you have rectal bleeding or fail to have a bowel movement after use of a laxative. These could be signs of a serious condition.
- you need to use a laxative for more than 1 week

If pregnant or breast-feeding,

ask a health professional before use.

Keep out of reach of children.

In case of overdose, get medical help or contact a Poison Control Center right away.

Directions

- take with a glass of water

adults and children 12 years and over | take 1 to 3 tablets in a single daily dose
children 6 to under 12 years | take 1 tablet in a single daily dose
children under 6 years | ask a doctor

Other information

- TAMPER EVIDENT: DO NOT USE IF OUTER PACKAGE IS OPENED OR BLISTER IS TORN OR BROKEN
- avoid excessive humidity
- store at 25°C (77°F); excursions permitted between 15°-30°C (59°-86°F)
- see end flap for expiration date and lot number

Inactive ingredients

carmine, colloidal silicon dioxide, corn starch, FD&C red #40 aluminum lake, hypromellose, lactose anhydrous, magnesium stearate, methacrylic acid, microcrystalline cellulose, polydextrose, polyethylene glycol, shellac wax, simethicone, sodium bicarbonate, sodium lauryl sulfate, stearic acid, talc, titanium dioxide, triacetin, triethyl citrate

Questions or comments?

1-800-426-9391

Principal display panel

QC®
Quality
Choice

NDC 63868-573-30

Women’s Gentle Laxative
Bisacodyl USP, 5 mg - Stimulant Laxative

Gentle, Dependable
Constipation Relief

30 Comfort Coated Tablets

Actual
Size

50844 ORG011967601

TAMPER EVIDENT: DO NOT USE IF
PACKAGE IS OPENED OR IF BLISTER
UNIT IS TORN, BROKEN OR SHOWS
ANY SIGNS OF TAMPERING

Distributed by: C.D.M.A., Inc,©
43157 W 9 Mile Rd
Novi, MI 48375
www.qualitychoice.com
Questions: 800-935-2362

SATISFACTION
GUARANTEED
100%
QC

Quality Choice 44-676A